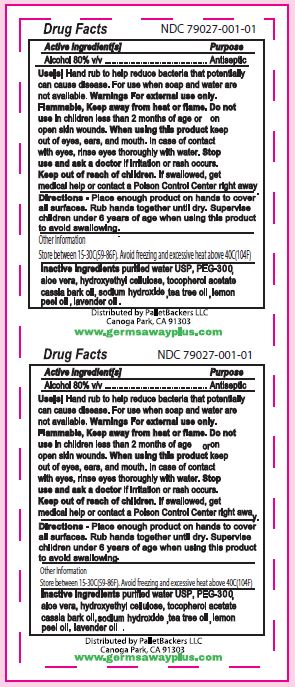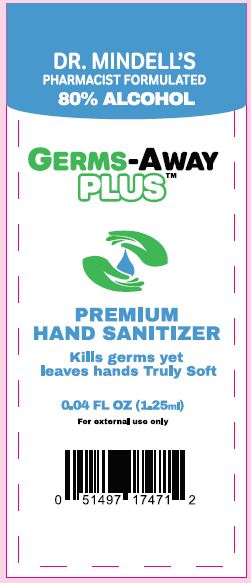 DRUG LABEL: Hand Sanitizer
NDC: 79027-001 | Form: LIQUID
Manufacturer: Savvy Wellness
Category: otc | Type: HUMAN OTC DRUG LABEL
Date: 20200629

ACTIVE INGREDIENTS: ALCOHOL 80 mL/100 mL
INACTIVE INGREDIENTS: .ALPHA.-TOCOPHEROL ACETATE 0.01 mL/100 mL; SODIUM HYDROXIDE 0.03 mL/100 mL; WATER 15.98 mL/100 mL; HYDROXYETHYL CELLULOSE, UNSPECIFIED 1.06 mL/100 mL; POLYETHYLENE GLYCOL 300 1.46 mL/100 mL; ALOE VERA LEAF 1.46 mL/100 mL

Savvy Wellness Germs-Awa Plus Hand Sanitizing Gel

This is a gel hand sanitizer manufactured using only United States Pharmacopoeia (USP) grade ingredients in the preparation of the product.

Active Ingredient(s)

Alcohol 80% v/v.

Purpose

Antiseptic

Use

Hand rub to help reduce bacteria that potentially can cause disease. For use when soap and water are not available.

Warnings

For external use only. Flammable. Keep away from heat or flame

Do not use

In children less than 2 months of age and on open skin wound.

When using this product keep out of eyes, ears, and mouth. In case of contact with eyes, rinse eyes thoroughly with water.

Stop use and ask a doctor if irritation or rash occurs. These may be signs of a serious condition.

Keep out of reach of children. If swallowed, get medical help or contact a Poison Control Center right away.

Directions

- Place enough product on hands to cover all surfaces. Rub hands together until dry.
- Supervise children under 6 years of age when using this product to avoid swallowing.

Other information

- Store between 15-30C (59-86F)
- Avoid freezing and excessive heat above 40C (104F)

Inactive ingredients

Purified water USP, PEG 300, aloe vera, hydroxyethyl cellulose, sodium hydroxide, tocopheral acetate, cassia bark oil, lavender oil, tea tree oil, lemon peel oil.

Package Label - Principal Display Panel

1.25 mL NDC: 79027-001-01